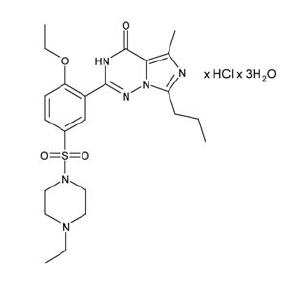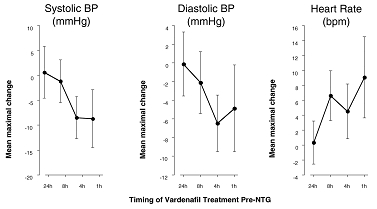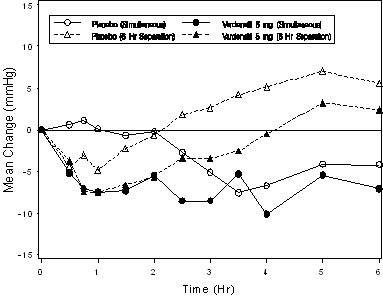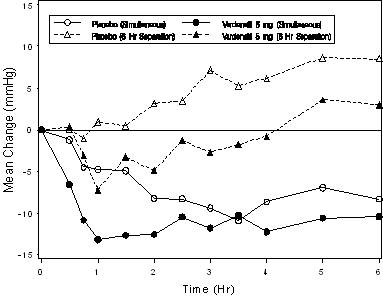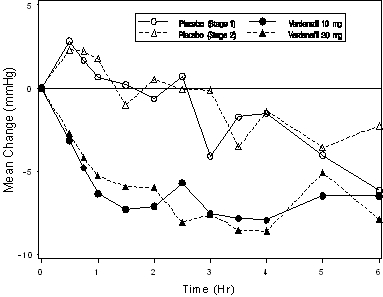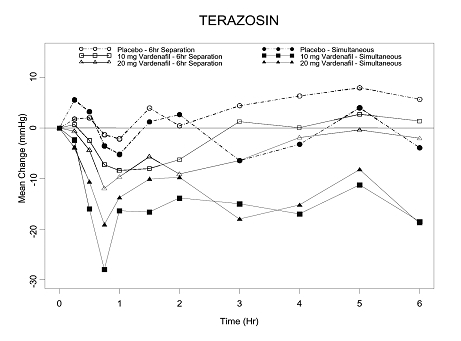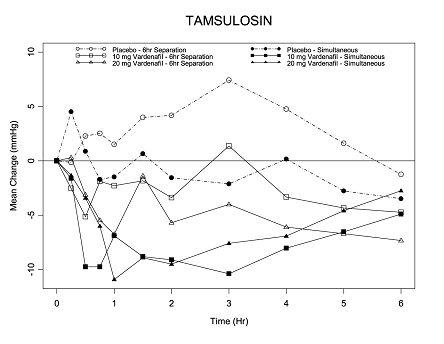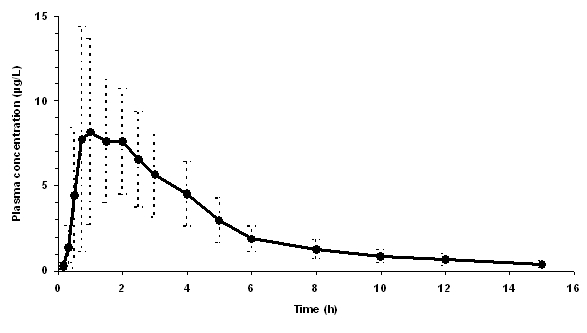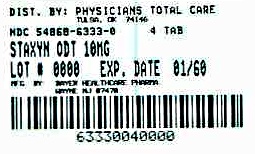 DRUG LABEL: Staxyn
NDC: 54868-6333 | Form: TABLET, ORALLY DISINTEGRATING
Manufacturer: Physicians Total Care, Inc.
Category: prescription | Type: HUMAN PRESCRIPTION DRUG LABEL
Date: 20120423

ACTIVE INGREDIENTS: VARDENAFIL HYDROCHLORIDE 10 mg/1 1
INACTIVE INGREDIENTS: ASPARTAME; MAGNESIUM STEARATE; CROSPOVIDONE; MANNITOL; SILICON DIOXIDE; SORBITOL

HIGHLIGHTS OF PRESCRIBING INFORMATION

These highlights do not include all the information needed to use Staxyn safely and effectively. See full prescribing information for Staxyn.
STAXYN (vardenafil hydrochloride) orally disintegrating tablets
Initial U.S. Approval: 2003

1 INDICATIONS AND USAGE

- STAXYN is a phosphodiesterase 5 (PDE5) inhibitor indicated for the treatment of erectile dysfunction. (1)

2 DOSAGE AND ADMINISTRATION

- STAXYN is not interchangeable with vardenafil 10 mg film-coated tablets (LEVITRA). STAXYN provides higher systemic exposure compared to vardenafil 10 mg film-coated tablets (LEVITRA). (2.1)
- STAXYN is taken as needed, orally, approximately 60 minutes before sexual activity. (2.1)
- The maximum recommended dosing frequency is one tablet per day. (2.1)
- STAXYN should be placed on the tongue where it will disintegrate. It should be taken without liquid. (2.1)
- STAXYN may be taken with or without food. (2.2)

3 DOSAGE FORMS AND STRENGTHS

- STAXYN 10 mg: White, round, orally disintegrating tablets (not scored) (3)

4 CONTRAINDICATIONS

- Administration with nitrates and nitric oxide donors (2.4, 4.1)

5 WARNINGS AND PRECAUTIONS

- Cardiovascular Effects: Patients should not use STAXYN if sex is inadvisable due to cardiovascular status. (5.1)
- Potent and Moderate CYP3A4 Inhibitors: Do not use STAXYN in patients taking potent or moderate CYP3A4 inhibitors. (5.2, 7.2)
- Risk of Priapism: In the event that an erection lasts more than 4 hours, the patient should seek immediate medical assistance. (5.3)
- Effects on the Eye: Patients should stop use of STAXYN, and seek medical attention in the event of sudden loss of vision in one or both eyes. Discuss with patients the increased risk of non-arteritic anterior ischemic optic neuropathy (NAION) in individuals who have already experienced NAION. (5.4, 6.2)
- Sudden Hearing Loss: Patients should stop STAXYN and seek medical attention in the event of sudden decrease or loss in hearing. (5.5, 6.2)
- Alpha-Blockers: Caution is advised when PDE5 inhibitors are co-administered with alpha-blockers. In some patients, concomitant use of these two drug classes can lower blood pressure significantly leading to symptomatic hypotension (for example, fainting). In patients taking alpha-blockers, do not initiate vardenafil therapy with STAXYN. (2.4, 5.6)
- QT Prolongation: Patients with congenital QT syndrome or taking class IA or III antiarrhythmics should avoid using STAXYN. (5.7, 12.2)
- Phenylketonurics: Each STAXYN tablet contains 1.01 mg phenylalanine per tablet, which could be harmful for patients with phenylketonuria. (5.12)

6 ADVERSE REACTIONS

Adverse reactions reported by ≥ 2% of patients treated with STAXYN: Headache, flushing, nasal congestion, dyspepsia, dizziness, back pain. (6.1)

To report SUSPECTED ADVERSE REACTIONS, contact Bayer
HealthCare Pharmaceuticals at 1-888-84-BAYER (1-888-842-2937) or
FDA at 1-800-FDA-1088 or www.fda.gov/medwatch

7 DRUG INTERACTIONS

- STAXYN can potentiate the hypotensive effects of nitrates, alpha-blockers, and antihypertensives. (7.1)
- Do not use STAXYN with moderate or potent CYP3A4 inhibitors as co-administration will result in significant increases in plasma vardenafil concentrations. (7.2)

8 USE IN SPECIFIC POPULATIONS

- Do not use STAXYN in patients with moderate or severe hepatic impairment. (8.6)
- Do not use STAXYN in patients on renal dialysis. (8.7)

FULL PRESCRIBING INFORMATION

1 INDICATIONS AND USAGE

STAXYN™ is indicated for the treatment of erectile dysfunction.

2 DOSAGE AND ADMINISTRATION

2.1 General

STAXYN is available in 10 mg orally disintegrating tablets. STAXYN is not interchangeable with vardenafil 10 mg film-coated tablets (LEVITRA). STAXYN provides higher systemic exposure compared to vardenafil 10 mg film-coated tablets (LEVITRA). [See Clinical Pharmacology (12.3).]

STAXYN should be taken orally, as needed, approximately 60 minutes before sexual activity. The maximum dosing frequency is one STAXYN tablet per day. Sexual stimulation is required for a response to treatment.

STAXYN should be placed on the tongue where it will disintegrate. The tablet should be taken without liquid. It should be taken immediately upon removal from the blister.

Those patients who require a lower or higher dose of vardenafil need to be prescribed vardenafil film-coated tablets [see Patient Counseling Information (17.11)].

2.2 Use with Food

STAXYN can be taken with or without food.

2.3 Use in Special Populations

Hepatic Impairment: Do not use STAXYN in patients with moderate (Child-Pugh B) or severe (Child-Pugh C) hepatic impairment [see Warnings and Precautions (5.8) and Clinical Pharmacology (12.3)].

Renal Impairment: Do not use STAXYN in patients on renal dialysis [see Warnings and Precautions (5.9) and Clinical Pharmacology (12.3)].

2.4 Concomitant Medications

Nitrates: Concomitant use with nitrates in any form is contraindicated [see Contraindications (4.1)].

CYP3A4 Inhibitors: Do not use STAXYN with potent or moderate CYP3A4 inhibitors such as ketoconazole, itraconazole, ritonavir, indinavir, saquinavir, atazanavir, clarithromycin and erythromycin [see Warnings and Precautions (5.2) and Drug Interactions (7.2)].

Alpha-Blockers: In those patients who are stable on alpha-blocker therapy, PDE5 inhibitors should be initiated at the lowest recommended starting dose. In patients taking alpha-blockers, do not initiate vardenafil therapy with STAXYN. Lower doses of vardenafil film-coated tablets should be used as initial therapy in these patients. [see Dosage and Administration (2.4)]. Patients taking alpha-blockers who have previously used vardenafil film-coated tablets may change to STAXYN at the advice of their healthcare provider. [See Warnings and Precautions (5.6) and Drug Interactions (7.1).]

3 DOSAGE FORMS AND STRENGTHS

STAXYN is available in 10 mg white, round, orally disintegrating tablets (not scored), no debossing.

4 CONTRAINDICATIONS

4.1 Nitrates

Administration of STAXYN with nitrates (either regularly and/or intermittently) and nitric oxide donors is contraindicated [see Clinical Pharmacology (12.2)]. Consistent with the effects of PDE5 inhibition on the nitric oxide/cyclic guanosine monophosphate pathway, PDE5 inhibitors, including STAXYN, may potentiate the hypotensive effects of nitrates. A suitable time interval following STAXYN dosing for the safe administration of nitrates or nitric oxide donors has not been determined.

5 WARNINGS AND PRECAUTIONS

The evaluation of erectile dysfunction should include a medical assessment, a determination of potential underlying causes and the identification of appropriate treatment.

Before prescribing STAXYN, it is important to note the following:

5.1 Cardiovascular effects

General

Physicians should consider the cardiovascular status of their patients, since there is a degree of cardiac risk associated with sexual activity. Therefore, treatment for erectile dysfunction, including STAXYN, should not be used in men for whom sexual activity is not recommended because of their underlying cardiovascular status.

There are no controlled clinical data on the safety or efficacy of vardenafil in the following patients; and therefore its use is not recommended until further information is available: unstable angina; hypotension (resting systolic blood pressure of <90 mmHg); uncontrolled hypertension (>170/110 mmHg); recent history of stroke, life-threatening arrhythmia, or myocardial infarction (within the last 6 months); severe cardiac failure.

Left Ventricular Outflow Obstruction

Patients with left ventricular outflow obstruction (for example, aortic stenosis and idiopathic hypertrophic subaortic stenosis) can be sensitive to the action of vasodilators including PDE5 inhibitors.

Blood Pressure Effects

Vardenafil has systemic vasodilatory properties that resulted in transient decreases in supine blood pressure in healthy volunteers (mean maximum decrease of 7 mmHg systolic and 8 mmHg diastolic) [see Clinical Pharmacology (12.2)]. While this normally would be expected to be of little consequence in most patients, prior to prescribing STAXYN, physicians should carefully consider whether their patients with underlying cardiovascular disease could be affected adversely by such vasodilatory effects.

5.2 Potential for Drug Interactions with Potent or Moderate CYP3A4 Inhibitors

Concomitant administration with potent CYP3A4 inhibitors (such as ritonavir, indinavir, ketoconazole) or moderate CYP3A4 inhibitors (such as erythromycin) increases plasma concentrations of vardenafil. Do not use STAXYN in patients taking potent or moderate CYP3A4 inhibitors. [See Dosage and Administration (2.4), Drug Interactions (7.2) and Patient Counseling Information (17.11).]

5.3 Risk of Priapism

There have been rare reports of prolonged erections greater than 4 hours and priapism (painful erections greater than 6 hours in duration) for this class of compounds, including vardenafil. In the event that an erection persists longer than 4 hours, the patient should seek immediate medical assistance. If priapism is not treated immediately, penile tissue damage and permanent loss of potency may result.

STAXYN should be used with caution by patients with anatomical deformation of the penis (such as angulation, cavernosal fibrosis, or Peyronie’s disease) or by patients who have conditions that may predispose them to priapism (such as sickle cell anemia, multiple myeloma, or leukemia).

5.4 Effects on the Eye

Physicians should advise patients to stop use of all PDE5 inhibitors, including STAXYN, and seek medical attention in the event of sudden loss of vision in one or both eyes. Such an event may be a sign of non-arteritic anterior ischemic optic neuropathy (NAION), a cause of decreased vision, including permanent loss of vision, that has been reported rarely postmarketing in temporal association with the use of all PDE5 inhibitors. It is not possible to determine whether these events were related directly to the use of PDE5 inhibitors or to other factors. Physicians should also discuss with patients the increased risk of NAION in individuals who have already experienced NAION in one eye, including whether such individuals could be adversely affected by use of vasodilators such as PDE5 inhibitors [see Adverse Reactions (6.2)].

STAXYN has not been evaluated in patients with known hereditary degenerative retinal disorders, including retinitis pigmentosa, therefore its use is not recommended until further information is available in those patients.

5.5 Sudden Hearing Loss

Physicians should advise patients to stop taking all PDE5 inhibitors, including STAXYN, and seek prompt medical attention in the event of sudden decrease or loss of hearing. These events, which may be accompanied by tinnitus and dizziness, have been reported in temporal association to the intake of PDE5 inhibitors, including vardenafil. It is not possible to determine whether these events are related directly to the use of PDE5 inhibitors or to other factors [see Adverse Reactions (6.2)].

5.6 Alpha-Blockers

In patients taking alpha-blockers, do not initiate vardenafil therapy with STAXYN. Patients treated with alpha-blockers who have previously used vardenafil film-coated tablets may be changed to STAXYN at the advice of their healthcare provider. Caution is advised when PDE5 inhibitors are co-administered with alpha-blockers. PDE5 inhibitors, including STAXYN, and alpha-adrenergic blocking agents are both vasodilators with blood-pressure lowering effects. When vasodilators are used in combination, an additive effect on blood pressure may be anticipated. In some patients, concomitant use of these two drug classes can lower blood pressure significantly [see Drug Interactions (7.1) and Clinical Pharmacology (12.2)] leading to symptomatic hypotension (for example, fainting). Consideration should be given to the following:

- Patients should be stable on alpha-blocker therapy prior to initiating a PDE5 inhibitor. Patients who demonstrate hemodynamic instability on alpha-blocker therapy alone are at increased risk of symptomatic hypotension with concomitant use of PDE5 inhibitors.
- In those patients who are stable on alpha-blocker therapy, PDE5 inhibitors should be initiated at the lowest recommended starting dose. In patients taking alpha-blockers, do not initiate vardenafil therapy with STAXYN. Lower doses of vardenafil film-coated tablets should be used as initial therapy in these patients [see Dosage and Administration (2.4)].
- In those patients already taking an optimized dose of PDE5 inhibitor, alpha-blocker therapy should be initiated at the lowest dose. Stepwise increases in alpha-blocker dose may be associated with further lowering of blood pressure in patients taking a PDE5 inhibitor.
- Safety of combined use of PDE5 inhibitors and alpha-blockers may be affected by other variables, including intravascular volume depletion and other anti-hypertensive drugs.

5.7 Congenital or Acquired QT Prolongation

In a study of the effect of vardenafil on QT interval in 59 healthy males [see Clinical Pharmacology (12.2)], therapeutic (10 mg film-coated tablets) and supratherapeutic (80 mg) doses of vardenafil and the active control moxifloxacin (400 mg) produced similar increases in QTc interval. A postmarketing study evaluating the effect of combining vardenafil with another drug of comparable QT effect showed an additive QT effect when compared with either drug alone [see Clinical Pharmacology (12.2)]. These observations should be considered in clinical decisions when prescribing vardenafil to patients with known history of QT prolongation or patients who are taking medications known to prolong the QT interval.

Patients taking Class 1A (for example, quinidine, procainamide) or Class III (for example, amiodarone, sotalol) antiarrhythmic medications or those with congenital QT prolongation, should avoid using STAXYN .

5.8 Hepatic Impairment

Do not use STAXYN in patients with moderate (Child-Pugh B) or severe (Child-Pugh C) hepatic impairment [see Dosage and Administration (2.3) Clinical Pharmacology (12.3)] and Use in Specific Populations (8.6)].

5.9 Renal Impairment

Do not use STAXYN in patients on renal dialysis, as vardenafil has not been evaluated in this population [see Dosage and Administration (2.3) and Use in Specific Populations (8.7)].

5.10 Combination with Other Erectile Dysfunction Therapies

The safety and efficacy of STAXYN used in combination with other treatments for erectile dysfunction have not been studied. Therefore, the use of such combinations is not recommended.

5.11 Effects on Bleeding

In humans, vardenafil film-coated tablet alone in doses up to 20 mg does not prolong the bleeding time. There is no clinical evidence of any additive prolongation of the bleeding time when vardenafil is administered with aspirin. STAXYN has not been administered to patients with bleeding disorders or significant active peptic ulceration. Therefore STAXYN should be administered to these patients after careful benefit-risk assessment.

5.12 Phenylketonurics

STAXYN contains aspartame, a source of phenylalanine which may be harmful for people with phenylketonuria.

Phenylketonurics: Each STAXYN tablet contains 1.01 mg phenylalanine per tablet.

5.13 Fructose Intolerance

STAXYN contains sorbitol. Patients with rare hereditary problems of fructose intolerance should not take STAXYN.

5.14 Sexually Transmitted Disease

The use of STAXYN offers no protection against sexually transmitted diseases. Counseling of patients about protective measures necessary to guard against sexually transmitted diseases, including the Human Immunodeficiency Virus (HIV), should be considered.

6 ADVERSE REACTIONS

The following serious adverse reactions with the use of STAXYN (vardenafil) are discussed elsewhere in the labeling:

- Cardiovascular effects [see Contraindications (4.1) and Warnings and Precautions (5.1)]
- Priapism [see Warnings and Precautions (5.3)]
- QT Prolongation [see Warnings and Precautions (5.7)]
- Effects on eye [see Warnings and Precautions (5.4)]
- Sudden hearing loss [see Warnings and Precautions (5.5)]

6.1 Clinical Studies Experience

Because clinical trials are conducted under widely varying conditions, adverse reaction rates observed in the clinical trials of a drug cannot be directly compared to rates in the clinical trials of another drug and may not reflect the rates observed in practice.

STAXYN: Safety of STAXYN was evaluated in two identical multi-national, randomized, double-blind, placebo-controlled trials. In both pivotal studies, enrollment was stratified so that approximately 50% of patients were ≥65 years old. Approximately 8% (n=29) were ≥75 years old. An integrated analysis of both studies included a total of 355 subjects that received STAXYN compared to 340 subjects that received placebo (mean age was 61.7, range 21.0 to 88.0; 68% White, 5% Black, 6% Asian, 11% Hispanic and 11% Other). The discontinuation rates due to adverse reactions were 1.4% for STAXYN compared to 0.6% for placebo. Table 1 below details the most frequently reported adverse reactions.

Table 1: Adverse drug reactions reported by ≥2% of the patients treated with STAXYN and more frequent on drug than placebo in controlled trials
Adverse Drug Reaction | STAXYN; (n=355) | Placebo; (n=340)
Headache | 14.4% | 1.8%
Flushing | 7.6% | 0.6%
Nasal Congestion | 3.1% | 0.3%
Dyspepsia | 2.8% | 0%
Dizziness | 2.3% | 0%
Back Pain | 2% | 0.3%

Adverse drug reactions reported in the STAXYN placebo controlled trials were comparable to the adverse drug reactions reported in earlier vardenafil film-coated tablets placebo controlled trials.

All Vardenafil Studies: Vardenafil film-coated tablets and STAXYN has been administered to over 17,000 men (mean age 54.5, range 18–89 years; 70% White, 5% Black, 13% Asian, 4% Hispanic and 8% Other) during controlled and uncontrolled clinical trials worldwide. The number of patients treated for 6 months or longer was 3357, and 1350 patients were treated for at least 1 year.

In the placebo-controlled clinical trials for vardenafil film-coated tablets and STAXYN, the discontinuation rate due to adverse events was 1.9% for vardenafil compared to 0.8% for placebo.

Placebo-controlled trials suggested a dose effect in the incidence of some adverse reactions (for example, dizziness, headache, flushing, dyspepsia, nausea, nasal congestion) over the 5 mg, 10 mg, and 20 mg doses of vardenafil film-coated tablets.

The following section identifies additional, less frequent adverse reactions (<2%) reported during the clinical development of vardenafil film-coated tablets and STAXYN. Excluded from this list are those adverse reactions that are infrequent and minor, those events that may be commonly observed in the absence of drug therapy, and those events that are not reasonably associated with the drug:

Body as a whole: allergic edema and angioedema, feeling unwell, allergic reactions, chest pain

Auditory: tinnitus, vertigo

Cardiovascular: palpitation, tachycardia, angina pectoris, myocardial infarction, ventricular tachyarrhythmias, hypotension

Digestive: nausea, gastrointestinal and abdominal pain, dry mouth, diarrhea, gastroesophageal reflux disease, gastritis, vomiting, increase in transaminases

Musculoskeletal: increase in creatine phosphokinase (CPK), increased muscle tone and cramping, myalgia

Nervous: paresthesia and dysesthesia, somnolence, sleep disorder, syncope, amnesia, seizure

Respiratory: dyspnea, sinus congestion

Skin and appendages: erythema, rash

Ophthalmologic: visual disturbance, ocular hyperemia, visual color distortions, eye pain and eye discomfort, photophobia, increase in intraocular pressure, conjunctivitis

Urogenital: increase in erection, priapism

6.2 Postmarketing Experience

The following adverse reactions have been identified during post approval use of vardenafil in the film-coated tablet formulation. Because these reactions are reported voluntarily from a population of uncertain size, it is not always possible to estimate their frequency or establish a causal relationship to drug exposure.

Ophthalmologic: Non-arteritic anterior ischemic optic neuropathy (NAION), a cause of decreased vision including permanent loss of vision, has been reported rarely postmarketing in temporal association with the use of PDE5 inhibitors, including vardenafil. Most, but not all, of these patients had underlying anatomic or vascular risk factors for development of NAION, including but not necessarily limited to: low cup to disc ratio (“crowded disc”), age over 50, diabetes, hypertension, coronary artery disease, hyperlipidemia and smoking. It is not possible to determine whether these events are related directly to the use of PDE5 inhibitors, to the patient’s underlying vascular risk factors or anatomical defects, to a combination of these factors, or to other factors [see Warnings and Precautions (5.4) and Patient Counseling Information (17.8)].

Visual disturbances including vision loss (temporary or permanent), such as visual field defect, retinal vein occlusion, and reduced visual acuity, have also been reported rarely in postmarketing experience. It is not possible to determine whether these events are related directly to the use of vardenafil.

Neurologic: Seizure, seizure recurrence and transient global amnesia have been reported postmarketing in temporal association with vardenafil.

Otologic: Cases of sudden decrease or loss of hearing have been reported postmarketing in temporal association with the use of PDE5 inhibitors, including vardenafil. In some cases, medical conditions and other factors were reported that may have also played a role in the otologic adverse events. In many cases, medical follow-up information was limited. It is not possible to determine whether these reported events are related directly to the use of vardenafil, to the patient’s underlying risk factors for hearing loss, a combination of these factors, or to other factors [see Patient Counseling Information (17.9)].

7 DRUG INTERACTIONS

The drug interaction studies described below were conducted using vardenafil film-coated tablets.

7.1 Potential for Pharmacodynamic Interactions with STAXYN

Nitrates: Concomitant use of STAXYN and nitrates is contraindicated. The blood pressure lowering effects of sublingual nitrates (0.4 mg) taken 1 and 4 hours after vardenafil and increases in heart rate when taken at 1, 4 and 8 hours after vardenafil were potentiated by a 20 mg dose of vardenafil in healthy middle-aged subjects. These effects were not observed when vardenafil 20 mg was taken 24 hours before the nitroglycerin (NTG). Potentiation of the hypotensive effects of nitrates for patients with ischemic heart disease has not been evaluated, and concomitant use of STAXYN and nitrates is contraindicated [see Contraindications (4.1) and Clinical Pharmacology (12.2)].

Alpha-Blockers: Patients taking alpha-blockers should not initiate vardenafil therapy with STAXYN. Patients treated with alpha-blockers who have previously used vardenafil film-coated tablets may be switched to STAXYN at the advice of their healthcare provider. Caution is advised when PDE5 inhibitors are co-administered with alpha-blockers. PDE5 inhibitors, including STAXYN and alpha-adrenergic blocking agents are both vasodilators with blood-pressure-lowering effects. When vasodilators are used in combination, an additive effect on blood pressure may be anticipated. Clinical pharmacology studies have been conducted with co-administration of vardenafil with terazosin or tamsulosin. [See Dosage and Administration (2.4), Warnings and Precautions (5.6), and Clinical Pharmacology (12.2).]

Antihypertensives: STAXYN may add to the blood pressure lowering effect of antihypertensive agents. In a clinical pharmacology study of patients with erectile dysfunction, single doses of 20 mg vardenafil caused a mean maximum decrease in supine blood pressure of 7 mmHg systolic and 8 mmHg diastolic (compared to placebo), accompanied by a mean maximum increase of heart rate of 4 beats per minute. The maximum decrease in blood pressure occurred between 1 and 4 hours after dosing. Following multiple dosing for 31 days, similar blood pressure responses were observed on Day 31 as on Day 1.

Alcohol: Vardenafil 20 mg did not potentiate the hypotensive effects of alcohol during the 4-hour observation period in healthy volunteers when administered with alcohol (0.5 g/kg body weight: approximately 40 mL of absolute alcohol in a 70 kg person). Alcohol and vardenafil plasma levels were not altered when dosed simultaneously.

7.2 Effect of Other Drugs on Vardenafil

In vitro studies

Studies in human liver microsomes showed that vardenafil is metabolized primarily by cytochrome P450 (CYP) isoforms 3A4/5, and to a lesser degree by CYP2C9. Therefore, inhibitors of these enzymes are expected to reduce vardenafil clearance [see Dosage and Administration (2.4) and Warnings and Precautions (5.2)].

In vivo studies

Do not use STAXYN with moderate and potent CYP3A4 inhibitors such as erythromycin, grapefruit juice, clarithromycin, ketoconazole, itraconazole, indinavir, saquinavir, atazanavir, ritonavir as the systemic concentration of vardenafil is increased in their presence [see Warnings and Precautions (5) and Dosage and Administration (2.4)].

Potent CYP3A4 inhibitors

Ketoconazole (200 mg once daily) produced a 10-fold increase in vardenafil area under the curve (AUC) and a 4-fold increase in maximum concentration (Cmax) when co-administered with vardenafil 5 mg in healthy volunteers. [See Dosage and Administration (2.4) and Warnings and Precautions (5).]

Indinavir (800 mg t.i.d.) co-administered with vardenafil 10 mg resulted in a 16-fold increase in vardenafil AUC, a 7-fold increase in vardenafil Cmax and a 2-fold increase in vardenafil half-life. [See Dosage and Administration (2.4) and Warnings and Precautions (5).]

Ritonavir (600 mg b.i.d.) co-administered with vardenafil 5 mg resulted in a 49-fold increase in vardenafil AUC and a 13-fold increase in vardenafil Cmax. The interaction is a consequence of blocking hepatic metabolism of vardenafil by ritonavir, a highly potent CYP3A4 inhibitor, which also inhibits CYP2C9. [See Dosage and Administration (2.4) and Warnings and Precautions (5).]

Moderate CYP3A4 inhibitors

Erythromycin (500 mg t.i.d.) produced a 4-fold increase in vardenafil AUC and a 3-fold increase in vardenafil Cmax when co-administered with vardenafil 5 mg in healthy volunteers [see Dosage and Administration (2) and Warnings and Precautions (5)].

Other Drug Interactions

No pharmacokinetic interactions were observed between vardenafil and the following drugs: glyburide, warfarin, digoxin, an antacid based on magnesium-aluminum hydroxide, and ranitidine. In the warfarin study, vardenafil had no effect on the prothrombin time or other pharmacodynamic parameters.

Cimetidine (400 mg b.i.d.) had no effect on AUC and Cmax of vardenafil when co-administered with 20 mg vardenafil in healthy volunteers.

7.3 Effects of Vardenafil on Other Drugs

In vitro studies

Vardenafil and its metabolites had no effect on CYP1A2, 2A6, and 2E1 (Ki >100 micromolar). Weak inhibitory effects toward other isoforms (CYP2C8, 2C9, 2C19, 2D6, 3A4) were found, but Ki values were in excess of plasma concentrations achieved following dosing. The most potent inhibitory activity was observed for vardenafil metabolite M1, which had a Ki of 1.4 micromolar toward CYP3A4, which is about 20 times higher than the M1 Cmax values after an 80 mg vardenafil dose.

In vivo studies

Nifedipine: Vardenafil 20 mg, when co-administered with slow-release nifedipine 30 mg or 60 mg once daily, did not affect the relative AUC or Cmax of nifedipine, a drug that is metabolized via CYP3A4. Nifedipine did not alter the plasma levels of vardenafil when taken in combination. In these patients whose hypertension was controlled with nifedipine, vardenafil 20 mg produced mean additional supine systolic/diastolic blood pressure reductions of 6/5 mmHg compared to placebo.

Ritonavir and Indinavir: Upon concomitant administration of 5 mg vardenafil with 600 mg b.i.d. ritonavir, the Cmax and AUC of ritonavir were reduced by approximately 20%. Upon administration of 10 mg of vardenafil (film-coated tablets) with 800 mg t.i.d. indinavir, the Cmax and AUC of indinavir were reduced by 40% and 30%, respectively.

Aspirin: Vardenafil 10 mg and 20 mg did not potentiate the increase in bleeding time caused by aspirin (two 81 mg tablets).

Other Interactions: Vardenafil had no effect on the pharmacodynamics of glyburide (glucose and insulin concentrations) and warfarin (prothrombin time or other pharmacodynamic parameters).

8 USE IN SPECIFIC POPULATIONS

8.1 Pregnancy

Pregnancy Category B: STAXYN is not indicated for use in women. There are no studies of STAXYN use in pregnant women.

No evidence of specific potential for teratogenicity, embryotoxicity or fetotoxicity was observed in rats and rabbits that received vardenafil at up to 18 mg/kg/day during organogenesis. This dose is approximately 100 fold (rat) and 29 fold (rabbit) greater than the AUC values for unbound vardenafil and its major metabolite in humans given the maximum recommended human dose (MRHD) of 20 mg.

In the rat pre-and postnatal development study, the NOAEL (no observed adverse effect level) for maternal toxicity was 8 mg/kg/day. Retarded physical development of pups in the absence of maternal effects was observed following maternal exposure to 1 and 8 mg/kg possibly due to vasodilatation and/or secretion of the drug into milk. The number of living pups born to rats exposed pre- and postnatally was reduced at 60 mg/kg/day. Based on the results of the pre- and postnatal study, the developmental NOAEL is less than 1 mg/kg/day. Based on plasma exposures in the rat developmental toxicity study, 1 mg/kg/day in the pregnant rat is estimated to produce total AUC values for unbound vardenafil and its major metabolite comparable to the human AUC at the MRHD of 20 mg. There are no adequate and well-controlled trials of vardenafil in pregnant women.

8.3 Nursing Mothers

STAXYN is not indicated for use in women. It is not known if vardenafil is excreted in human breast milk.

Vardenafil was secreted into the milk of lactating rats at concentrations approximately 10-fold greater than found in the plasma. Following a single oral dose of 3 mg/kg, 3.3% of the administered dose was excreted into the milk within 24 hours.

8.4 Pediatric Use

STAXYN is not indicated for use in pediatric patients. Safety and efficacy in children has not been established.

8.5 Geriatric Use

Vardenafil AUC and Cmax in elderly patients (65 years or older) taking STAXYN were increased by 39% and 21%, respectively, in comparison to patients aged 45 years and below. No overall differences in safety or effectiveness were observed between patients ≥65 years old and those < 65 years old in placebo-controlled clinical trials [see Clinical Pharmacology (12.3)].

8.6 Hepatic Impairment

Do not use STAXYN in patients with moderate or severe hepatic impairment.

In volunteers with mild hepatic impairment (Child-Pugh A), the Cmax and AUC following a 10 mg vardenafil (film-coated tablets) dose were increased by 22% and 17%, respectively, compared to healthy control subjects. STAXYN can be used in patients with mild hepatic impairment. In volunteers with moderate hepatic impairment (Child-Pugh B), the Cmax and AUC following a 10 mg vardenafil (film-coated tablets) dose were increased by 130% and 160%, respectively, compared to healthy control subjects. Vardenafil has not been evaluated in patients with severe (Child-Pugh C) hepatic impairment. Do not use STAXYN in patients with moderate to severe hepatic impairment. [See Warnings and Precautions (5.8) and Dosage and Administration (2).]

8.7 Renal Impairment

Do not use STAXYN in patients on renal dialysis.

In volunteers with mild renal impairment (CLcr = 50–80 mL/min), the pharmacokinetics of vardenafil 20 mg film-coated tablets were similar to those observed in a control group with normal renal function. In the moderate (CLcr = 30–50 mL/min) or severe (CLcr <30 mL/min) renal impairment groups, the AUC of vardenafil was 20–30% higher compared to that observed in a control group with normal renal function (CLcr >80 mL/min). STAXYN can be used in patients with mild, moderate or severe renal impairment. Do not use STAXYN in patients on renal dialysis as vardenafil has not been evaluated in such patients [see Dosage and Administration (2.3) and Warnings and Precautions (5.9)].

10 OVERDOSAGE

The maximum dose of vardenafil for which human data are available is a single 120 mg dose of the film–coated tablets administered to eight healthy male volunteers. The majority of these subjects experienced reversible back pain/myalgia and/or “abnormal vision.”

In cases of overdose, standard supportive measures should be taken as required. Renal dialysis is not expected to accelerate clearance because vardenafil is highly bound to plasma proteins and is not significantly eliminated in the urine.

11 DESCRIPTION

STAXYN is an oral therapy for the treatment of erectile dysfunction. This monohydrochloride salt of vardenafil is a selective inhibitor of cyclic guanosine monophosphate (cGMP)-specific PDE5.

Vardenafil HCl is designated chemically as piperazine, 1-[[3-(1,4-dihydro-5-methyl-4-oxo-7-propylimidazo[5,1-f][1,2,4]triazin-2-yl)-4-ethoxyphenyl]sulfonyl]-4-ethyl-, monohydrochloride and has the following structural formula:

Vardenafil HCl is a nearly colorless, solid substance with a molecular weight of 579.1 g/mol and a solubility of 0.11 mg/mL in water.

STAXYN is formulated as white round orally disintegrating tablets with no debossing. Each tablet contains 11.85 mg vardenafil hydrochloride, which corresponds to 10 mg vardenafil, and the following inactive ingredients: aspartame, peppermint flavor, magnesium stearate, and Pharmaburst™ B2 (crospovidone, mannitol, silica colloidal hydrated, and sorbitol).

12 CLINICAL PHARMACOLOGY

12.1 Mechanism of Action

Penile erection is a hemodynamic process initiated by the relaxation of smooth muscle in the corpus cavernosum and its associated arterioles. During sexual stimulation, nitric oxide is released from nerve endings and endothelial cells in the corpus cavernosum. Nitric oxide activates the enzyme guanylate cyclase resulting in increased synthesis of cyclic guanosine monophosphate (cGMP) in the smooth muscle cells of the corpus cavernosum. The cGMP in turn triggers smooth muscle relaxation, allowing increased blood flow into the penis, resulting in erection. The tissue concentration of cGMP is regulated by both the rates of synthesis and degradation via phosphodiesterases (PDEs). The most abundant PDE in the human corpus cavernosum is the cGMP-specific PDE5; therefore, the inhibition of PDE5 enhances erectile function by increasing the amount of cGMP. Because sexual stimulation is required to initiate the local release of nitric oxide, the inhibition of PDE5 has no effect in the absence of sexual stimulation.

In vitro studies have shown that vardenafil is a selective inhibitor of PDE5. The inhibitory effect of vardenafil is more selective on PDE5 than for other known phosphodiesterases (>15-fold relative to PDE6, >130-fold relative to PDE1, >300-fold relative to PDE11, and >1,000-fold relative to PDE2, 3, 4, 7, 8, 9, and 10).

12.2 Pharmacodynamics

The pharmacodynamic studies described below were conducted using vardenafil film-coated tablets.

Effects on Blood Pressure

In a clinical pharmacology study of patients with erectile dysfunction, single doses of vardenafil 20 mg film-coated tablets caused a mean maximum decrease in supine blood pressure of 7 mmHg systolic and 8 mmHg diastolic (compared to placebo), accompanied by a mean maximum increase of heart rate of 4 beats per minute. The maximum decrease in blood pressure occurred between 1 and 4 hours after dosing. Following multiple dosing for 31 days, similar blood pressure responses were observed on Day 31 as on Day 1. Vardenafil may add to the blood pressure lowering effects of antihypertensive agents [see Drug Interactions (7)].

Effects on Blood Pressure and Heart Rate when Vardenafil is Combined with Nitrates

A study was conducted in which the blood pressure and heart rate response to 0.4 mg nitroglycerin (NTG) sublingually was evaluated in 18 healthy subjects following pretreatment with vardenafil 20 mg film-coated tablets at various times before NTG administration. Vardenafil 20 mg caused an additional time-related reduction in blood pressure and increase in heart rate in association with NTG administration. The blood pressure effects were observed when vardenafil 20 mg was dosed 1 or 4 hours before NTG and the heart rate effects were observed when 20 mg was dosed 1, 4, or 8 hours before NTG. Additional blood pressure and heart rate changes were not detected when vardenafil 20 mg film-coated tablet was dosed 24 hours before NTG (see Figure 1).

Figure 1: Placebo-subtracted point estimates (with 90% CI) of mean maximal blood pressure and heart rate effects of pre-dosing with vardenafil 20 mg at 24, 8, 4, and 1 hour before 0.4 mg NTG sublingually

Because the disease state of patients requiring nitrate therapy is anticipated to increase the likelihood of hypotension, the use of vardenafil by patients on nitrate therapy or on nitric oxide donors is contraindicated [see Contraindications (4.1)].

Blood Pressure Effects in Patients on Stable Alpha-Blocker Treatment

Two clinical pharmacology studies were conducted in patients with benign prostatic hyperplasia (BPH) on stable-dose alpha-blocker treatment for at least four weeks.

Study 1: This study was designed to evaluate the effect of 5 mg vardenafil film-coated tablets compared to placebo when administered to BPH patients on chronic alpha-blocker therapy in two separate cohorts: tamsulosin 0.4 mg daily (cohort 1, n=21) and terazosin 5 or 10 mg daily (cohort 2, n=21). The design was a randomized, double blind, cross-over study with four treatments: vardenafil 5 mg or placebo administered simultaneously with the alpha-blocker and vardenafil 5 mg or placebo administered 6 hours after the alpha-blocker. Blood pressure and pulse were evaluated over the 6-hour interval after vardenafil dosing. For blood pressure (BP) results, see Table 2. One patient, after simultaneous treatment with 5 mg vardenafil and 10 mg terazosin, exhibited symptomatic hypotension with standing blood pressure of 80/60 mmHg occurring one hour after administration and subsequent mild dizziness and moderate lightheadedness lasting for 6 hours. For vardenafil and placebo, five and two patients, respectively, experienced a decrease in standing systolic blood pressure (SBP) of >30 mmHg following simultaneous administration of terazosin. Hypotension was not observed when vardenafil 5 mg and terazosin were administered 6 hours apart. Following simultaneous administration of vardenafil 5 mg and tamsulosin, two patients had a standing SBP of <85 mmHg; two and one patient (vardenafil and placebo, respectively) had a decrease in standing SBP of >30 mmHg. When tamsulosin and vardenafil 5 mg were separated by 6 hours, two patients had a standing SBP <85 mmHg and one patient had a decrease in SBP of >30 mmHg. There were no severe adverse events related to hypotension reported during the study. There were no cases of syncope.

Table 2: Mean (95% CI) maximal change from baseline in systolic blood pressure (mmHg) following vardenafil 5 mg in BPH patients on stable alpha-blocker therapy (study 1)
Alpha-Blocker |  | Simultaneous dosing of Vardenafil 5 mg and Alpha-Blocker, Placebo-Subtracted | Dosing of Vardenafil 5 mg and Alpha-Blocker Separated by 6 Hours, Placebo-Subtracted
Terazosin 5 or 10 mg daily | Standing SBP | -3 (-6.7, 0.1) | -4 (-7.4, -0.5)
Terazosin 5 or 10 mg daily | Supine SBP | -4 (-6.7, -0.5) | -4 (-7.1, -0.7)
Tamsulosin 0.4 mg daily | Standing SBP | -6 (-9.9, -2.1) | -4 (-8.3, -0.5)
Tamsulosin 0.4 mg daily | Supine SBP | -4 (-7, -0.8) | -5 (-7.9, -1.7)

Blood pressure effects (standing SBP) in normotensive men on stable dose tamsulosin 0.4 mg following simultaneous administration of vardenafil 5 mg or placebo, or following administration of vardenafil 5 mg or placebo separated by 6 hours are shown in Figure 2. Blood pressure effects (standing SBP) in normotensive men on stable dose terazosin (5 or 10 mg) following simultaneous administration of vardenafil 5 mg or placebo, or following administration of vardenafil 5 mg or placebo separated by 6 hours, are shown in Figure 3.

Figure 2: Mean change from baseline in standing systolic blood pressure (mmHg) over 6 hour interval following simultaneous or 6 hr separation administration of vardenafil 5 mg or placebo with stable dose tamsulosin 0.4 mg in normotensive BPH patients (study 1)
Figure 3: Mean change from baseline in standing systolic blood pressure (mmHg) over 6 hour interval following simultaneous or 6 hr separation administration of vardenafil 5 mg or placebo with stable dose terazosin (5 or 10 mg) in normotensive BPH patients (study 1)

Study 2: This study was designed to evaluate the effect of 10 mg vardenafil (film-coated tablets) (stage 1) and 20 mg vardenafil (film-coated tablets) (stage 2) compared to placebo, when administered to a single cohort of BPH patients (n=23) on stable therapy with tamsulosin 0.4 mg or 0.8 mg daily for at least four weeks. The design was a randomized, double blind, two-period, cross-over study. Vardenafil or placebo was given simultaneously with tamsulosin. Blood pressure and pulse were evaluated over the 6-hour interval after vardenafil dosing. For BP results see Table 3. One patient experienced a decrease from baseline in standing SBP of >30 mmHg following vardenafil 10 mg. There were no other instances of outlier blood pressure values (standing SBP <85 mmHg or decrease from baseline in standing SBP of >30 mmHg). Three patients reported dizziness following vardenafil 20 mg. There were no cases of syncope.

Table 3: Mean (95% CI) maximal change from baseline in systolic blood pressure (mmHg) following vardenafil 10 and 20 mg (film-coated tablets) in BPH patients on stable alpha-blocker therapy with tamsulosin 0.4 or 0.8 mg daily (study 2)
 | Vardenafil 10 mg Placebo-subtracted | Vardenafil 20 mg Placebo-subtracted
Standing SBP | -4 (-6.8, -0.3) | -4 (-6.8, -1.4)
Supine SBP | -5 (-8.2, -0.8) | -4 (-6.3, -1.8)

Blood pressure effects (standing SBP) in normotensive men on stable dose tamsulosin 0.4 mg following simultaneous administration of vardenafil 20 mg or placebo, or following administration of vardenafil 20 mg or placebo separated by 6 hours are shown in Figure 4.

Figure 4: Mean change from baseline in standing systolic blood pressure (mmHg) over 6 hour interval following simultaneous administration of vardenafil 10 mg film-coated tablet (stage 1), vardenafil 20 mg film-coated tablet (Stage 2), or placebo with stable dose tamsulosin 0.4 mg in normotensive BPH patients (study 2)

Blood Pressure Effects in Normotensive Men After Forced Titration with Alpha-Blockers

Two randomized, double blind, placebo-controlled clinical pharmacology studies with healthy normotensive volunteers (age range, 45–74 years) were performed after forced titration of the alpha-blocker terazosin to 10 mg daily over 14 days (n=29), and after initiation of tamsulosin 0.4 mg daily for five days (n=24). There were no severe adverse events related to hypotension in either study. Symptoms of hypotension were a cause for withdrawal in 2 subjects receiving terazosin and in 4 subjects receiving tamsulosin. Instances of outlier blood pressure values (defined as standing SBP <85 mmHg and/or a decrease from baseline of standing SBP >30 mmHg) were observed in 9/24 subjects receiving tamsulosin and 19/29 receiving terazosin. The incidence of subjects with standing SBP <85 mmHg given vardenafil and terazosin to achieve simultaneously the amount of time at the maximum concentration in serum (Tmax) led to early termination of that arm of the study. In most (7/8) of these subjects, instances of standing SBP <85 mmHg were not associated with symptoms. Among subjects treated with terazosin, outlier values were observed more frequently when vardenafil and terazosin were given to achieve simultaneous Tmax than when dosing was administered to separate Tmax by 6 hours. There were 3 cases of dizziness observed with concomitant administration of terazosin and vardenafil. Seven subjects experienced dizziness mainly occurring with simultaneous Tmax administration of tamsulosin. There were no cases of syncope.

Table 4: Mean (95% CI) maximal change in baseline in systolic blood pressure (mmHg) following vardenafil 10 and 20 mg (film-coated tablets) in healthy volunteers on daily alpha-blocker therapy
 |  | Dosing of Vardenafil and Alpha-Blocker Separated by 6 Hours |  | Simultaneous dosing of Vardenafil and Alpha-Blocker
Alpha-Blocker |  | Vardenafil 10 mg Placebo-Subtracted | Vardenafil 20 mg Placebo-Subtracted | Vardenafil 10 mg Placebo-Subtracted | Vardenafil 20 mg Placebo-Subtracted
Terazosin 10 mg daily | Standing SBP | -7 (-10, -3) | -11 (-14, -7) | -23 (-31, 16)* | -14 (-33, 11)*
Terazosin 10 mg daily | Supine SBP | -5 (-8, -2) | -7 (-11, -4) | -7 (-25, 19)* | -7 (-31, 22)*
Tamsulosin 0.4 mg daily | Standing SBP | -4 (-8, -1) | -8 (-11, -4) | -8 (-14, -2) | -8 (-14, -1)
Tamsulosin 0.4 mg daily | Supine SBP | -4 (-8, 0) | -7 (-11, -3) | -5 (-9, -2) | -3 (-7, 0)

* Due to the sample size, confidence intervals may not be an accurate measure for these data. These values represent the range for the difference.

Figure 5: Mean change from baseline in standing systolic blood pressure (mmHg) over 6 hour interval following simultaneous or 6 hr separation administration of vardenafil 10 mg and 20 mg (film-coated tablets) or placebo with terazosin (10 mg) in healthy volunteers

Figure 6: Mean change from baseline in standing systolic blood pressure (mmHg) over 6 hour interval following simultaneous or 6 hr separation administration of vardenafil 10 mg and 20 mg (film-coated tablets) or placebo with tamsulosin (0.4 mg) in healthy volunteers

Effects on Cardiac Electrophysiology

The effect of 10 mg and 80 mg vardenafil, administered as film-coated tablets, on QT interval was evaluated in a single-dose, double-blind, randomized, placebo- and active-controlled (moxifloxacin 400 mg) crossover study in 59 healthy males (81% White, 12% Black, 7% Hispanic) aged 45–60 years. The QT interval was measured at one hour post dose because this time point approximates the average time of peak vardenafil concentration. The 80 mg dose of vardenafil (four times the highest recommended dose of the film-coated tablets) was chosen because this dose yields plasma concentrations covering those observed upon co-administration of a low-dose of vardenafil (5 mg) and 600 mg b.i.d. of ritonavir. Of the CYP3A4 inhibitors that have been studied, ritonavir causes the most significant drug-drug interaction with vardenafil. Table 5 summarizes the effect on mean uncorrected QT and mean corrected QT interval (QTc) with different methods of correction (Fridericia and a linear individual correction method) at one hour post-dose. No single correction method is known to be more valid than the other. In this study, the mean increase in heart rate associated with a 10 mg dose of vardenafil, administered as a film-coated tablet, compared to placebo was 5 beats/minute and with an 80 mg dose of vardenafil the mean increase was 6 beats/minute.

Table 5: Mean QT and QTc changes in msec (90% CI) from baseline relative to placebo at 1 hour post-dose with different methodologies to correct for the effect of heart rate
Drug/Dose | QT Uncorrected (msec) | Fridericia QT Correction (msec) | Individual QT Correction (msec)
Vardenafil 10 mg | -2 (-4, 0) | 8 (6, 9) | 4 (3, 6)
Vardenafil 80 mg | -2 (-4, 0) | 10 (8, 11) | 6 (4, 7)
Moxifloxacin* 400 mg | 3 (1, 5) | 8 (6, 9) | 7 (5, 8)

* Active control (drug known to prolong QT)

Therapeutic and supratherapeutic doses of vardenafil and the active control moxifloxacin produced similar increases in QTc interval. This study, however, was not designed to make direct statistical comparisons between the drugs or the dose levels. The clinical impact of these QTc changes is unknown [see Warnings and Precautions (5)].

In a separate postmarketing study of 44 healthy volunteers, single doses of 10 mg vardenafil (film-coated tablet) resulted in a placebo-subtracted mean change from baseline of QTcF (Fridericia correction) of 5 msec (90% CI: 2,8). Single doses of gatifloxacin 400 mg resulted in a placebo-subtracted mean change from baseline QTcF of 4 msec (90% CI: 1,7). When vardenafil 10mg (film-coated tablets) and gatifloxacin 400 mg were co-administered, the mean QTcF change from baseline was additive when compared to either drug alone and produced a mean QTcF change of 9 msec from baseline (90% CI: 6,11). The clinical impact of these QT changes is unknown [see Warnings and Precautions (5.7)].

Effects on Exercise Treadmill Test in Patients with Coronary Artery Disease (CAD)

In two independent trials that assessed 10 mg (n=41) and 20 mg (n=39) vardenafil (film-coated tablets), respectively, vardenafil did not alter the total treadmill exercise time compared to placebo. The patient population included men aged 40–80 years with stable exercise-induced angina documented by at least one of the following: 1) prior history of myocardial infarction (MI), coronary artery bypass graft (CABG), percutaneous transluminal coronary angioplasty (PTCA), or stenting (not within 6 months); 2) positive coronary angiogram showing at least 60% narrowing of the diameter of at least one major coronary artery; or 3) a positive stress echocardiogram or stress nuclear perfusion study.

Results of these studies showed that vardenafil did not alter the total treadmill exercise time compared to placebo (vardenafil 10 mg vs. placebo: 433±109 and 426±105 seconds, respectively; 20 mg vardenafil vs. placebo: 414±114 and 411±124 seconds, respectively). The total time to angina was not altered by vardenafil when compared to placebo (10 mg vardenafil vs. placebo: 291±123 and 292±110 seconds; 20 mg vardenafil vs. placebo: 354±137 and 347±143 seconds, respectively). The total time to 1 mm or greater ST-segment depression was similar to placebo in both the 10 mg and the 20 mg vardenafil groups (10 mg vardenafil vs. placebo: 380±108 and 334±108 seconds; 20 mg vardenafil vs. placebo: 364±101 and 366±105 seconds, respectively).

Effects on Eye

Single oral doses of phosphodiesterase inhibitors have demonstrated transient dose-related impairment of color discrimination (blue/green) using the Farnsworth-Munsell 100-hue (FM-100) test and reductions in electroretinogram (ERG) b-wave amplitudes, with peak effects near the time of peak plasma levels. These findings are consistent with the inhibition of PDE6 in rods and cones, which is involved in phototransduction in the retina. The findings were most evident one hour after administration, diminishing but still present 6 hours after administration. In a single dose study in 25 normal males, vardenafil (film-coated tablets) 40 mg, twice the maximum daily recommended dose, did not alter visual acuity, intraocular pressure, fundoscopic and slit lamp findings.

In another double-blind, placebo-controlled clinical trial, at least 15 doses of 20 mg vardenafil were administered over 8 weeks versus placebo to 52 males. Thirty-two (32) males (62% of the patients) completed the trial. Retinal function was measured by ERG and FM-100 test 2, 6 and 24 hours after dosing. The trial was designed to detect changes in retinal function that might occur in more than 10% of patients. Vardenafil did not produce clinically significant ERG or FM-100 effects in healthy men compared to placebo. Two patients on vardenafil in the trial reported episodes of transient cyanopsia (objects appear blue).

Effects on Sperm Motility Morphology

There was no effect on sperm motility or morphology after single 20 mg oral doses of vardenafil film-coated tablets in healthy volunteers.

12.3 Pharmacokinetics

The pharmacokinetics of vardenafil and its M1 metabolite from STAXYN have been evaluated in healthy male volunteers (18–50 years) and in young (18–45 years) and elderly (≥ 65 years) erectile dysfunction patients. Studies have shown that STAXYN provides higher systemic exposure of vardenafil compared to vardenafil 10 mg film-coated tablets.

Absorption

Figure 7: Vardenafil Plasma Concentration (Mean ± SD) Profile for STAXYN in men age 18-45 years with erectile dysfunction

The median time to reach Cmax (Tmax) in patients receiving STAXYN in the fasted state was 1.5 h [range: 0.75 – 2.5 h]. After administration of STAXYN to elderly (≥ 65 years) and young (18–45 years) patients with erectile dysfunction, mean vardenafil AUC was increased by 21 to 29%, respectively while mean Cmax was lower by 19% and 8%, respectively, in comparison to 10 mg vardenafil (film-coated tablets). In a study of healthy male volunteers (18–50 years), the mean Cmax and AUC of vardenafil from STAXYN were higher by 15% and 44%, respectively compared to 10 mg vardenafil film-coated tablets.

Vardenafil was not found to accumulate in plasma when STAXYN was dosed daily over ten days.

Effect of food: A high fat meal had no effect on vardenafil AUC and Tmax from STAXYN in healthy volunteers and reduced Cmax by 35%. Clinical trials for STAXYN were conducted without regard to meals. STAXYN can be taken with or without food.

Effect of water: When STAXYN was swallowed with water, the AUC of vardenafil was reduced by 29% and median Tmax was shortened by 60 minutes while Cmax was not affected. In clinical trials, dosing was done without water. STAXYN should be taken without liquid.

Distribution

The mean steady-state volume of distribution (Vss) for vardenafil is 208 L, indicating extensive tissue distribution. Vardenafil and its major circulating metabolite, M1, are highly bound to plasma proteins (about 95% for parent drug and M1). This protein binding is reversible and independent of total drug concentrations.

Following a single oral dose of 20 mg vardenafil film-coated tablet in healthy volunteers, a mean of 0.00018% of the administered dose was obtained in semen 1.5 hours after dosing.

Metabolism

Vardenafil is metabolized predominantly by the hepatic enzyme CYP3A4, with contribution from the CYP3A5 and CYP2C isoforms. The major circulating metabolite, M1, results from desethylation at the piperazine moiety of vardenafil. M1 is subject to further metabolism. The plasma concentration of M1 is approximately 26% that of the parent compound. This metabolite shows a phosphodiesterase selectivity profile similar to that of vardenafil and an in vitro inhibitory potency for PDE5 28% of that of vardenafil. Therefore, M1 accounts for approximately 7% of total pharmacologic activity.

Excretion

The mean terminal half-life of vardenafil in patients receiving STAXYN tablets varied between about 4–6 hours. The elimination half-life of the metabolite M1 is between 3 to 5 hours. After oral administration, vardenafil is excreted as metabolites predominantly in the feces (approximately 91–95% of administered oral dose) and to a lesser extent in the urine (approximately 2–6% of administered oral dose). Vardenafil is a high clearance drug with a plasma clearance of 56.4 L/h following intravenous administration.

Pharmacokinetics in Specific Populations

Pediatrics

STAXYN is not indicated for use in pediatric patients. Vardenafil trials were not conducted in the pediatric population.

Geriatrics

Vardenafil AUC and Cmax in elderly patients (65 years or older) taking STAXYN were increased by 39% and 21%, respectively, in comparison to patients aged 45 years and below [see Use in Specific Populations (8.5)].

Hepatic Impairment

In volunteers with mild hepatic impairment (Child-Pugh A), the Cmax and AUC following a 10 mg vardenafil (film-coated tablets) dose were increased by 22% and 17%, respectively, compared to healthy control subjects. In volunteers with moderate hepatic impairment (Child-Pugh B), the Cmax and AUC following a 10 mg vardenafil (film-coated tablets) dose were increased by 130% and 160%, respectively, compared to healthy control subjects. Vardenafil has not been evaluated in patients with severe (Child-Pugh C) hepatic impairment. [See Dosage and Administration (2.3), Warnings and Precautions (5.8), and Use in Specific Populations (8.6).]

Renal Impairment

In volunteers with mild renal impairment (CLcr = 50–80 mL/min), the pharmacokinetics of vardenafil were similar to those observed in a control group with normal renal function. In the moderate (CLcr = 30–50 mL/min) or severe (CLcr <30 mL/min) renal impairment groups, the AUC of vardenafil was 20–30% higher compared to that observed in a control group with normal renal function (CLcr >80 mL/min). Vardenafil pharmacokinetics have not been evaluated in patients requiring renal dialysis [see Dosage and Administration (2.3), Warnings and Precautions (5.9), and Use in Specific Populations (8.7)].

13 NONCLINICAL TOXICOLOGY

13.1 Carcinogenesis, Mutagenesis, Impairment of Fertility

Carcinogenesis

Vardenafil was not carcinogenic in rats and mice when administered daily for 24 months. In these studies systemic drug exposures (AUCs) for unbound (free) vardenafil and its major metabolite were approximately 400- and 170-fold for male and female rats, respectively, and 21-and 37-fold for male and female mice, respectively, the exposures observed in human males given the maximum recommended human dose (MRHD) of 20 mg.

Mutagenesis

Vardenafil was not mutagenic as assessed in either the in vitro bacterial Ames assay or the forward mutation assay in Chinese hamster V79 cells. Vardenafil was not clastogenic as assessed in either the in vitro chromosomal aberration test or the in vivo mouse micronucleus test.

Impairment of Fertility

Vardenafil did not impair fertility in male and female rats administered doses up to 100 mg/kg/day for 28 days prior to mating in males, and for 14 days prior to mating and through day 7 of gestation in females. In a corresponding 1-month rat toxicity study, this dose produced an AUC value for unbound vardenafil 200 fold greater than AUC in humans at the MRHD of 20 mg.

14 CLINICAL STUDIES

The efficacy and safety of STAXYN were evaluated in two identical multi-national, randomized, double-blind, placebo-controlled trials (studies 1 and 2). STAXYN was dosed without regard to meals on an as-needed basis in men with erectile dysfunction (ED), many of whom had multiple other medical conditions. In both pivotal studies, randomization was stratified so that approximately 50% of patients were ≥65 years old. Primary efficacy assessment was by means of the Erectile Function (EF) Domain score of the validated International Index of Erectile Function (IIEF) Questionnaire and two questions from the Sexual Encounter Profile (SEP) dealing with the ability to achieve vaginal penetration (SEP2), and the ability to maintain an erection long enough for successful intercourse (SEP3). The primary endpoints were assessed at 3 months.

Study 1 evaluated 355 mainly European (Belgium, France, Germany, Spain, South Africa, and Netherlands) patients (mean age 61.9; 67% White, 4% Black, 3% Asian, 26% Unknown). The mean baseline EF domain scores were 13 for both placebo and STAXYN groups. Study 2 evaluated 331 mainly North American (USA, Canada, Mexico, and Australia) patients (mean age 61.7; 69% White, 5% Black, 4% Asian, 22% Hispanic). The mean baseline EF domain scores were 12 for STAXYN and 13 for placebo.

In both studies STAXYN demonstrated clinically meaningful and statistically significant improvements over placebo in all 3 primary efficacy variables (see Table 6).

Table 6: Change from Baseline for the Primary Efficacy Variables in Studies 1 and 2
 | Study 1 |  |  | Study 2
 | Placebo | STAXYN | p-value | Placebo | STAXYN | p-value
EF Domain Score | (N=172) | (N=181) |  | (N=160) | (N=167)
Endpoint | 14 | 21 |  | 14 | 21
Change from baseline | 1.6 | 8.7 | <.0001 | 1.5 | 8.5 | <.0001
Insertion of Penis (SEP2) | (N=169) | (N=179) |  | (N=161) | (N=168)
Endpoint | 45% | 74% |  | 43% | 69%
Change from baseline | 6.9% | 35.9% | <.0001 | 4.8% | 30.8% | <.0001
Maintenance of Erection (SEP3) | (N=164) | (N=178) |  | (N=160) | (N=168)
Endpoint | 26% | 65% |  | 27% | 60%
Change from baseline | 11.6% | 51.6% | <.0001 | 12.4% | 45.9% | <.0001

14.1 Other Vardenafil Clinical Trials Using Film-Coated Tablets

Patients with ED and Diabetes Mellitus

Vardenafil demonstrated clinically meaningful and statistically significant improvement in erectile function in a prospective, fixed-dose [10 and 20 mg vardenafil film-coated tablets], double-blind, placebo-controlled trial of patients with diabetes mellitus (n=439; mean age 57 years, range 33–81; 80% White, 9% Black, 8% Hispanic, and 3% Other).

Significant improvements in the EF Domain were shown in this study (EF Domain scores of 17 on 10 mg vardenafil and 19 on 20 mg vardenafil compared to 13 on placebo; p <0.0001).

Vardenafil significantly improved the overall per-patient rate of achieving an erection sufficient for penetration (SEP2) (61% on 10 mg and 64% on 20 mg vardenafil compared to 36% on placebo; p <0.0001).

Vardenafil demonstrated a clinically meaningful and statistically significant increase in the overall per-patient rate of maintenance of erection to successful intercourse (SEP3) (49% on 10 mg, 54% on 20 mg vardenafil compared to 23% on placebo; p <0.0001).

Patients with ED after Radical Prostatectomy

Vardenafil demonstrated clinically meaningful and statistically significant improvement in erectile function in a prospective, fixed-dose 10 and 20 mg vardenafil film-coated tablets, double-blind, placebo-controlled trial in post-prostatectomy patients (n=427, mean age 60, range 44–77 years; 93% White, 5% Black, 2% Other).

Significant improvements in the EF Domain were shown in this study (EF Domain scores of 15 on 10 mg vardenafil and 15 on 20 mg vardenafil compared to 9 on placebo; p <0.0001).

Vardenafil significantly improved the overall per-patient rate of achieving an erection sufficient for penetration (SEP2) (47% on 10 mg and 48% on 20 mg vardenafil compared to 22% on placebo; p <0.0001).

Vardenafil demonstrated a clinically meaningful and statistically significant increase in the overall per-patient rate of maintenance of erection to successful intercourse (SEP3) (37% on 10 mg, 34% on 20 mg vardenafil compared to 10% on placebo; p <0.0001).

16 HOW SUPPLIED/STORAGE AND HANDLING

16.1 How Supplied

STAXYN (vardenafil HCl) are white, round orally disintegrating tablets with no debossing. STAXYN orally disintegrating tablets are packaged into foil blisterpacks and supplied as a 4 tablet unit or as a 40 tablet bulk pack.

Package | Strength | NDC Code
1 blister card containing 4 tablets | 10 mg | 54868-6333-0

In addition to the active ingredient, vardenafil, each tablet contains aspartame, peppermint flavor, magnesium stearate, and Pharmaburst™ B2 (crospovidone, mannitol, silica colloidal hydrated, and sorbitol).

16.2 Recommended Storage

Store STAXYN at 25°C (77°F); excursions permitted to 15–30°C (59–86°F) [see USP Controlled Room Temperature].

STAXYN is dispensed in blisterpacks. The patient should be advised to examine the blisterpack before use and not use if blisters are torn, broken, or missing.

17 PATIENT COUNSELING INFORMATION

See FDA-Approved Patient Labeling

17.1 Use with Other Formulations of Vardenafil

Physicians should inform patients that STAXYN is not interchangeable with vardenafil film-coated tablets (LEVITRA) as it provides higher systemic exposure. They should also discuss that the maximum dosage is one STAXYN tablet per 24 hours.

17.2 Nitrates

Physicians should discuss with patients the contraindication of STAXYN with regular and/or intermittent use of organic nitrates. Patients should be counseled that concomitant use of vardenafil with nitrates could cause blood pressure to suddenly drop to an unsafe level, resulting in dizziness, syncope, or even heart attack or stroke.

17.3 Cardiovascular

Physicians should discuss with patients the potential cardiac risk of sexual activity for patients with preexisting cardiovascular risk factors.

17.4 Concomitant Use with Drugs which Lower Blood Pressure

Physicians should inform their patients that in some patients concomitant use of PDE5 inhibitors, including STAXYN, with alpha-blockers can lower blood pressure significantly leading to symptomatic hypotension (for example, fainting). Patients who are taking alpha-blockers should only use STAXYN when previous treatment with vardenafil film-coated tablets has been well tolerated [see Dosage and Administration (2) and Drug Interactions (7)]. Patients should be advised of the possible occurrence of symptoms related to postural hypotension and appropriate countermeasures. Patients should be advised to contact the prescribing physician if other anti-hypertensive drugs or new medications that may interact with STAXYN are prescribed by another healthcare provider.

17.5 Recommended Administration

Physicians should discuss with patients the appropriate use of STAXYN and its anticipated benefits. It should be explained that sexual stimulation is required for an erection to occur after taking STAXYN. STAXYN should be taken approximately 60 minutes before sexual activity. Patients should be counseled regarding the dosing of STAXYN, especially regarding the maximum daily dose. Patients should be advised to contact their healthcare provider if they are not satisfied with the quality of their sexual performance with STAXYN or in the case of an unwanted effect.

17.6 Priapism

Physicians should inform patients that there have been rare reports of prolonged erections greater than 4 hours and priapism (painful erections greater than 6 hours in duration) for vardenafil and this class of compounds. In the event that an erection persists longer than 4 hours, the patient should seek immediate medical assistance. If priapism is not treated immediately, penile tissue damage and permanent loss of potency may result.

17.7 Drug Interactions

Patients should be advised to contact the prescribing physician if new medications that may interact with STAXYN are prescribed by another healthcare provider.

17.8 Vision

Physicians should advise patients to stop use of all PDE5 inhibitors, including STAXYN, and seek medical attention in the event of sudden loss of vision in one or both eyes. Such an event may be a sign of non-arteritic anterior ischemic optic neuropathy (NAION), a cause of decreased vision, including permanent loss of vision, that has been reported rarely postmarketing in temporal association with the use of all PDE5 inhibitors. It is not possible to determine whether these events were related directly to the use of PDE5 inhibitors or to other factors. Physicians should also discuss with patients the increased risk of NAION in individuals who have already experienced NAION in one eye, including whether such individuals could be adversely affected by use of vasodilators such as PDE5 inhibitors [see Adverse Reactions (6.1)].

17.9 Sudden Hearing Loss

Physicians should advise patients to stop taking PDE5 inhibitors, including STAXYN, and seek prompt medical attention in the event of sudden decrease or loss of hearing. These events, which may be accompanied by tinnitus and dizziness, have been reported in temporal association to the intake of PDE5 inhibitors, including STAXYN. It is not possible to determine whether these events are related directly to the use of PDE5 inhibitors or to other factors [see Adverse Reactions (6)].

17.10 Sexually Transmitted Disease

The use of STAXYN offers no protection against sexually transmitted diseases. Counseling of patients about protective measures necessary to guard against sexually transmitted diseases, including the Human Immunodeficiency Virus (HIV), should be considered.

17.11 Dose Adjustment

STAXYN is available only in a single strength. Patients who require a different dosage should be prescribed vardenafil film-coated tablets (LEVITRA).

FDA-Approved Patient Labeling

STAXYN™ (stax-in)

(vardenafil HCl)
orally disintegrating tablets

Read the Patient Information about STAXYN before you start taking it and again each time you get a refill. There may be new information. You may also find it helpful to share this information with your partner. This leaflet does not take the place of talking with your doctor. You and your doctor should talk about STAXYN when you start taking it and at regular checkups. If you do not understand the information, or have questions, talk with your doctor or pharmacist.

WHAT IMPORTANT INFORMATION SHOULD YOU KNOW ABOUT STAXYN?

STAXYN is not interchangeable with vardenafil film-coated tablets (LEVITRA).

STAXYN can cause your blood pressure to drop suddenly to an unsafe level if it is taken with certain other medicines. With a sudden drop in blood pressure, you could get dizzy, faint, or have a heart attack or stroke.

STAXYN contains phenylalanine which can be harmful to people who have phenylketonuria. Talk to your doctor if you have phenylketonuria.

Do not take STAXYN if you:

- Take any medicines called “nitrates” (often used to control chest pain, also known as angina)
- Use recreational drugs called “poppers” like amyl nitrate and butyl nitrate.

(See “Who Should Not Take STAXYN?”)

Tell all your healthcare providers that you take STAXYN. If you need emergency medical care for a heart problem, it will be important for your healthcare provider to know when you last took STAXYN.

WHAT IS STAXYN?

STAXYN is a prescription medicine taken by mouth for the treatment of erectile dysfunction (ED) in men.

ED is a condition where the penis does not harden and expand when a man is sexually excited, or when he cannot keep an erection. A man who has trouble getting or keeping an erection should see his doctor for help if the condition bothers him. STAXYN may help a man with ED get and keep an erection when he is sexually excited.

STAXYN does not:

- Cure ED.
- Increase a man’s sexual desire.
- Protect a man or his partner from sexually transmitted diseases, including HIV. Speak to your doctor about ways to guard against sexually transmitted diseases.
- Serve as a male form of birth control.

STAXYN is only for men with ED. STAXYN is not for women or children. STAXYN must be used only under a doctor’s care.

HOW DOES STAXYN WORK?

When a man is sexually stimulated, his body’s normal physical response is to increase blood flow to his penis. This results in an erection. STAXYN helps increase blood flow to the penis and may help men with ED get and keep an erection satisfactory for sexual activity. Once a man has completed sexual activity, blood flow to his penis decreases, and his erection goes away.

WHO CAN TAKE STAXYN?

Talk to your doctor to decide if STAXYN is right for you.

STAXYN has been shown to be effective in men over the age of 18 years who have erectile dysfunction, including men with diabetes.

WHO SHOULD NOT TAKE STAXYN?

Do not take STAXYN if you:

- Take any medicines called “nitrates” (see “What important information should you know about STAXYN?”). Nitrates are commonly used to treat angina. Angina is a symptom of heart disease and can cause pain in your chest, jaw, or down your arm.

Medicines called nitrates include nitroglycerin that is found in tablets, sprays, ointments, pastes, or patches. Nitrates can also be found in other medicines such as isosorbide dinitrate or isosorbide mononitrate. Some recreational drugs called “poppers” also contain nitrates, such as amyl nitrate and butyl nitrate. Do not use STAXYN if you are using these drugs. Ask your doctor or pharmacist if you are not sure if any of your medicines are nitrates.

- Have been told by your healthcare provider to not have sexual activity because of health problems. Sexual activity can put an extra strain on your heart, especially if your heart is already weak from a heart attack or heart disease.

WHAT SHOULD YOU DISCUSS WITH YOUR DOCTOR BEFORE TAKING STAXYN?

Before taking STAXYN, tell your doctor about all your medical problems, including if you:

- Have heart problems such as angina, heart failure, irregular heartbeats, or have had a heart attack. Ask your doctor if it is safe for you to have sexual activity.
- Have low blood pressure or have high blood pressure that is not controlled.
- Have had a stroke.
- Have had a seizure.
- Or any family members have a rare heart condition known as prolongation of the QT interval (long QT syndrome).
- Have liver problems.
- Have kidney problems and require dialysis.
- Have retinitis pigmentosa, a rare genetic (runs in families) eye disease.
- Have ever had severe vision loss, or if you have an eye condition called non-arteritic anterior ischemic optic neuropathy (NAION).
- Have stomach ulcers.
- Have a bleeding problem.
- Have a deformed penis shape or Peyronie’s disease.
- Have had an erection that lasted more than 4 hours.
- Have blood cell problems such as sickle cell anemia, multiple myeloma, or leukemia.
- Have hearing problems.
- Have phenylketonuria.
- Have fructose intolerance.

CAN OTHER MEDICATIONS AFFECT STAXYN?

Tell your doctor about all the medicines you take including prescription and non-prescription medicines, vitamins, and herbal supplements. STAXYN and other medicines may affect each other. Always check with your doctor before starting or stopping any medicines. Especially tell your doctor if you take any of the following:

- Medicines called nitrates (see “What important information should you know about STAXYN?”).
- Medicines that treat abnormal heartbeat. These include quinidine, procainamide, amiodarone and sotalol.
- Ritonavir (Norvir®) or indinavir sulfate (Crixivan®) saquinavir (Fortavase® or Invirase®) or atazanavir (Reyataz®) or other HIV protease inhibitors.
- Ketoconazole or itraconazole (such as Nizoral® or Sporanox®).
- Erythromycin or clarithromycin.
- Other medicines or treatments for ED.

Patients taking these drugs should not use STAXYN.

Patients taking alpha-blockers should not initiate vardenafil therapy with STAXYN. Patients taking alpha-blockers who have previously used vardenafil film-coated tablets may switch to STAXYN at the advice of their healthcare provider.

- Medicines called alpha-blockers. These include Hytrin® (terazosin HCl), Flomax® (tamsulosin HCl), Cardura® (doxazosin mesylate), Minipress® (prazosin HCl) or Uroxatral® (alfuzosin HCl), Rapaflo® (silodosin). Alpha-blockers are sometimes prescribed for prostate problems or high blood pressure. In some patients the use of PDE5 inhibitor drugs, including STAXYN, with alpha-blockers can lower blood pressure significantly leading to fainting.

HOW SHOULD YOU TAKE STAXYN?

Take STAXYN exactly as your doctor prescribes. STAXYN comes in 10 mg orally disintegrating tablets. The dose is one STAXYN tablet. Do not take more than one STAXYN a day. Doses should be taken at least 24 hours apart.

- If you have prostate problems or high blood pressure, for which you take medicines called alpha-blockers, you should not start treatment for erectile dysfunction with STAXYN. Your doctor may prescribe a lower dose of vardenafil film-coated tablet.

Take 1 STAXYN tablet about 1 hour (60 min) before sexual activity. Some form of sexual stimulation is needed for an erection to happen with STAXYN. STAXYN may be taken with or without meals.

Place on the tongue where it will dissolve rapidly. The tablet should be taken whole and not crushed or split.

The tablet should not be taken with liquid.

It should be taken immediately upon removal from the blister.

Call your doctor or emergency room immediately if you accidentally took more STAXYN than prescribed.

If you receive STAXYN in a blisterpack, examine the blisterpack before use. Do not use if blisters are torn, broken, or missing.

WHAT ARE THE POSSIBLE SIDE EFFECTS OF STAXYN?

The most common side effects with STAXYN are headache, flushing, stuffy or runny nose, indigestion, upset stomach, dizziness, and back pain. These side effects usually go away after a few hours. Call your doctor if you get a side effect that bothers you or one that will not go away.

STAXYN may uncommonly cause:

- An erection that won’t go away (priapism). If you get an erection that lasts more than 4 hours, get medical help right away. Priapism must be treated as soon as possible or lasting damage can happen to your penis including the inability to have erections.
- Color vision changes, such as seeing a blue tinge to objects or having difficulty telling the difference between the colors blue and green.

In rare instances, men taking PDE5 inhibitors (oral erectile dysfunction medicines, including vardenafil) reported a sudden decrease or loss of vision in one or both eyes. It is not possible to determine whether these events are related directly to these medicines, to other factors such as high blood pressure or diabetes, or to a combination of these. If you experience sudden decrease or loss of vision, stop taking PDE5 inhibitors, including STAXYN, and call a doctor right away.

Sudden loss or decrease in hearing, sometimes with ringing in the ears and dizziness, has been rarely reported in people taking PDE5 inhibitors, including vardenafil. It is not possible to determine whether these events are related directly to the PDE5 inhibitors, to other diseases or medications, to other factors, or to a combination of factors. If you experience these symptoms, stop taking STAXYN and contact a doctor right away.

These are not all the side effects of STAXYN. For more information, ask your doctor or pharmacist.

HOW SHOULD STAXYN BE STORED?

- Store STAXYN at room temperature between 59–86° F (15–30° C).
- Keep STAXYN and all medicines out of the reach of children.

GENERAL INFORMATION ABOUT STAXYN

Medicines are sometimes prescribed for conditions other than those described in patient information leaflets. Do not use STAXYN for a condition for which it was not prescribed. Do not give STAXYN to other people, even if they have the same symptoms that you have. It may harm them.

This leaflet summarizes the most important information about STAXYN. If you would like more information, talk with your healthcare provider. You can ask your doctor or pharmacist for information about STAXYN that is written for health professionals.

For more information you can also visit www.STAXYN.com or call 1-888-825-5249.

WHAT ARE THE INGREDIENTS OF STAXYN?

Active Ingredient: vardenafil hydrochloride

Inactive Ingredients of STAXYN: Aspartame, peppermint flavor, magnesium stearate and Pharmaburst™ B2 (crospovidone, mannitol, silica colloidal hydrated, and sorbitol)

Phenylketonurics: STAXYN contains 1.01 mg phenylalanine per tablet.

Products cited in STAXYN USPI

LEVITRA is a registered trademark of Bayer AG and is used under license by GlaxoSmithKline.

Norvir (ritonavir) is a trademark of Abbott Laboratories

Crixivan (indinavir sulfate) is a trademark of Merck & Co., Inc.

Invirase or Fortavase (saquinavir mesylate) is a trademark of Roche Laboratories Inc.

Reyataz (atazanavir sulfate) is a trademark of Bristol-Myers Squibb Company

Nizoral (ketoconazole) is a trademark of Johnson & Johnson

Sporanox (itraconazole) is a trademark of Johnson & Johnson

Hytrin (terazosin HCl) is a trademark of Abbott Laboratories

Flomax (tamsulosin HCl) is a trademark of Yamanouchi Pharmaceutical Co., Ltd.

Cardura (doxazosin mesylate) is a trademark of Pfizer Inc.

Minipress (prazosin HCl) is a trademark of Pfizer Inc.

Rapaflo (silodosin) is a trademark of Watson Pharma Inc.

Uroxatral (alfuzosin HCl) is a trademark of Sanofi-Synthelabo

Pharmaburst B2 is a trademark of SPI Pharma Inc.

Manufactured for:

Bayer HealthCare Pharmaceuticals Inc.
Wayne, NJ 07470

Made in Germany

Distributed by:

GlaxoSmithKline

Research Triangle Park

NC 27709

Rx Only

©2011 Bayer HealthCare Pharmaceuticals Inc.

Additional barcode labeling by:
Physicians Total Care, Inc.
Tulsa, Oklahoma 74146

PACKAGE LABEL

STAXYN 10 mg, 4 Tablet Carton

Rx only NDC 54868-6333-0

STAXYN™
(vardenafil hydrochloride)
orally disintegrating tablets

10 mg * PER TABLET

Place the orally disintegrating tablet in the mouth, on the tongue.

The orally disintegrating tablet should be taken without liquid.

Rx only

4 tablets